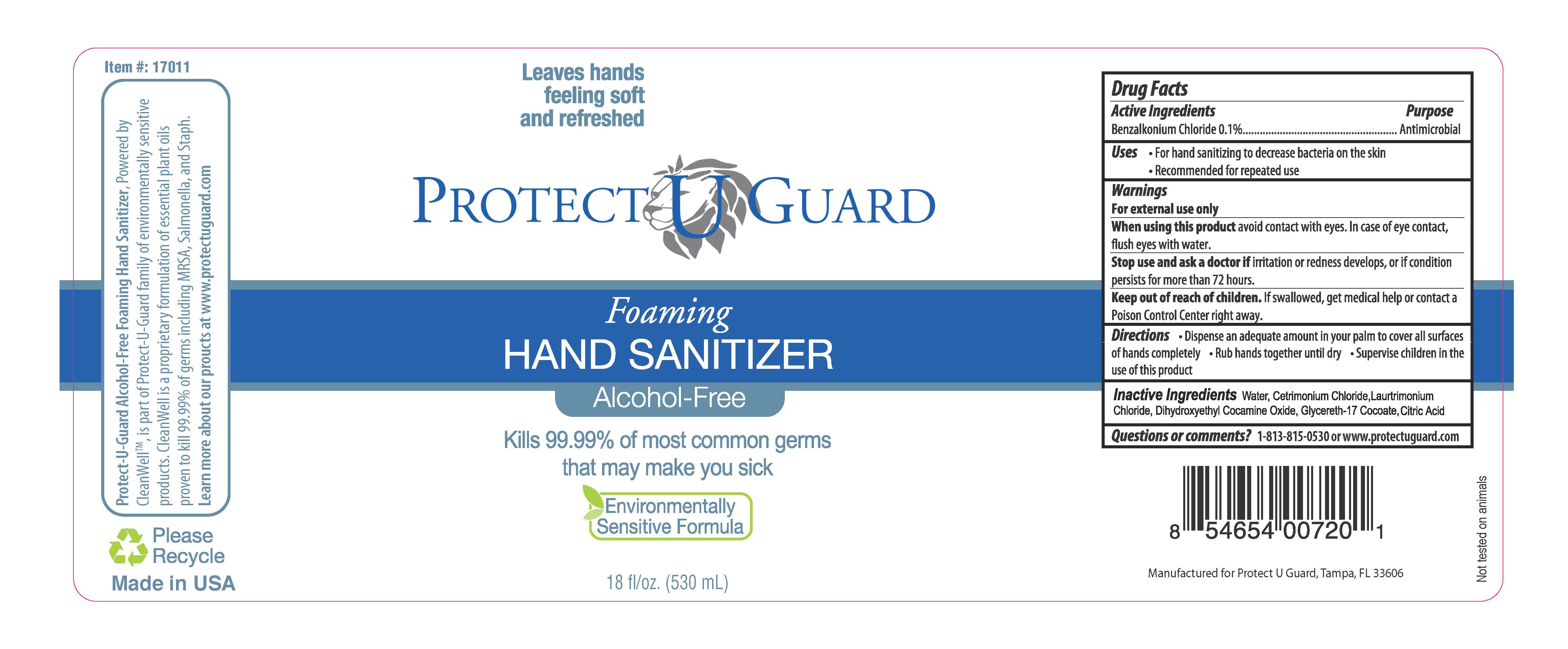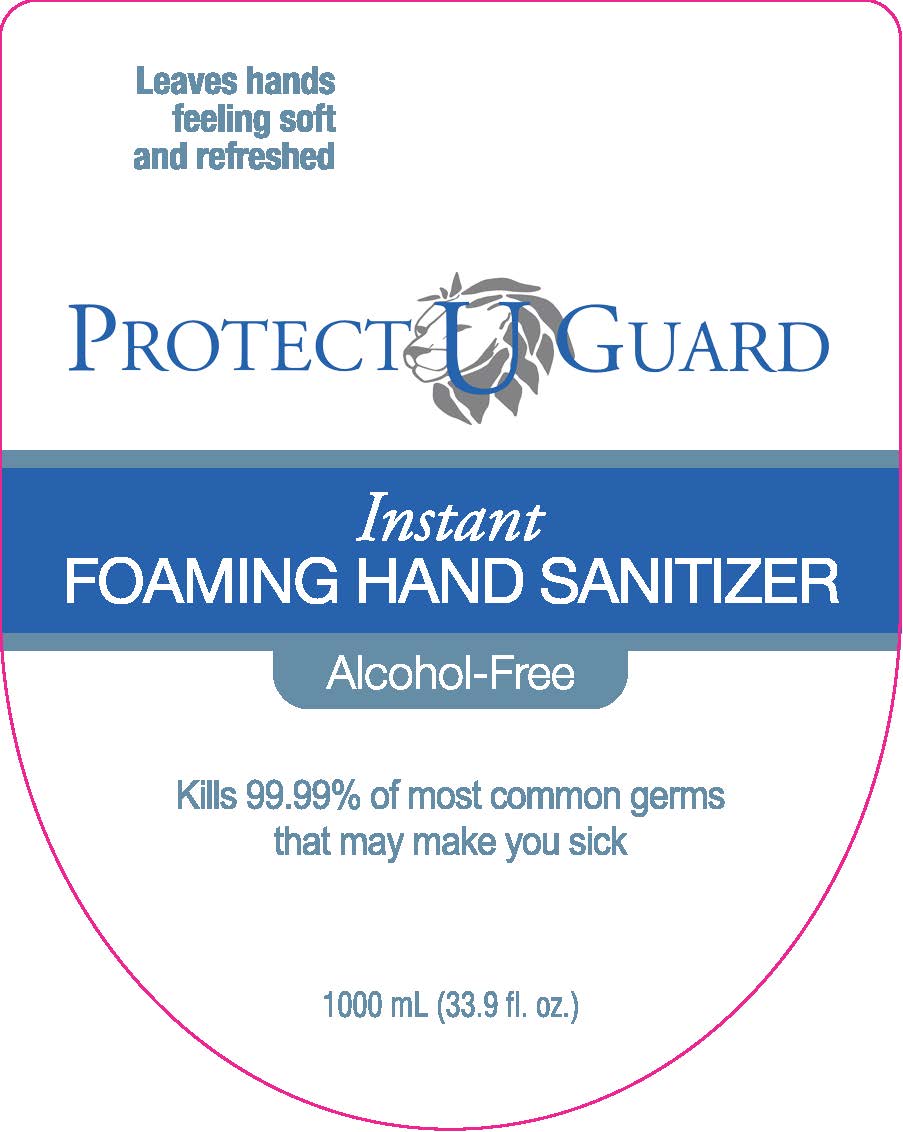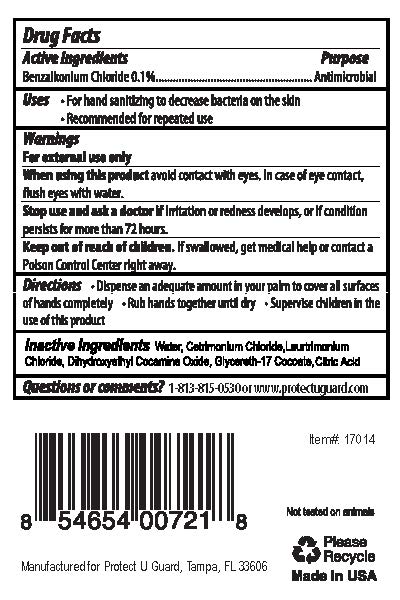 DRUG LABEL: Protect U Guard Foaming Hand Sanitizer Alcohol Free
NDC: 71788-234 | Form: LIQUID
Manufacturer: Protect U Guard, LLC
Category: otc | Type: HUMAN OTC DRUG LABEL
Date: 20171106

ACTIVE INGREDIENTS: BENZALKONIUM CHLORIDE 0.1 g/100 mL
INACTIVE INGREDIENTS: DIHYDROXYETHYL COCAMINE OXIDE; CETRIMONIUM CHLORIDE; LAURTRIMONIUM CHLORIDE; GLYCERETH-17 COCOATE; CITRIC ACID MONOHYDRATE

Active Ingredients

Benzalkonium Chloride 0.1%

Purpose

Antimicrobial

Uses

For hand sanitizing to decrease bacteria on the skin

Recommended for repeated use

Warnings

For external use only

When using this product avoid contact with eyes. In case of eye contact, flush eyes with water.

Stop use and aska a doctor if irritation or redness develops, or if condition persists for more than 72 hours.

Keep out of reach of chidren. If swallowed, get medical help or contacta a Poison Control Center right away.

When using this product avoid contact with eyes. In case of eye contact, flush eyes with water.

Stop use and ask a doctor if irritation or redness develops, or if condition persists for more than 72 hours.

Keep out of reach of children. If Swallowed, get medical help or contact a Poison Control Center right away.

Directions

Dispense an adequate amount in your palm to cover all surfaces of hands completely.

Rub hnads together until dry.

Supervise children in the use of this product.

Inactive Ingredients

Water, Cetrimonium Chloride, Laurtrimonium Chloride, Dihydroxyethyl Cocamine Oxide, Glycereth-17 Cocate, Citric Acid

Questions or comments?

1-813-815-0530 or www.protectuguard.com